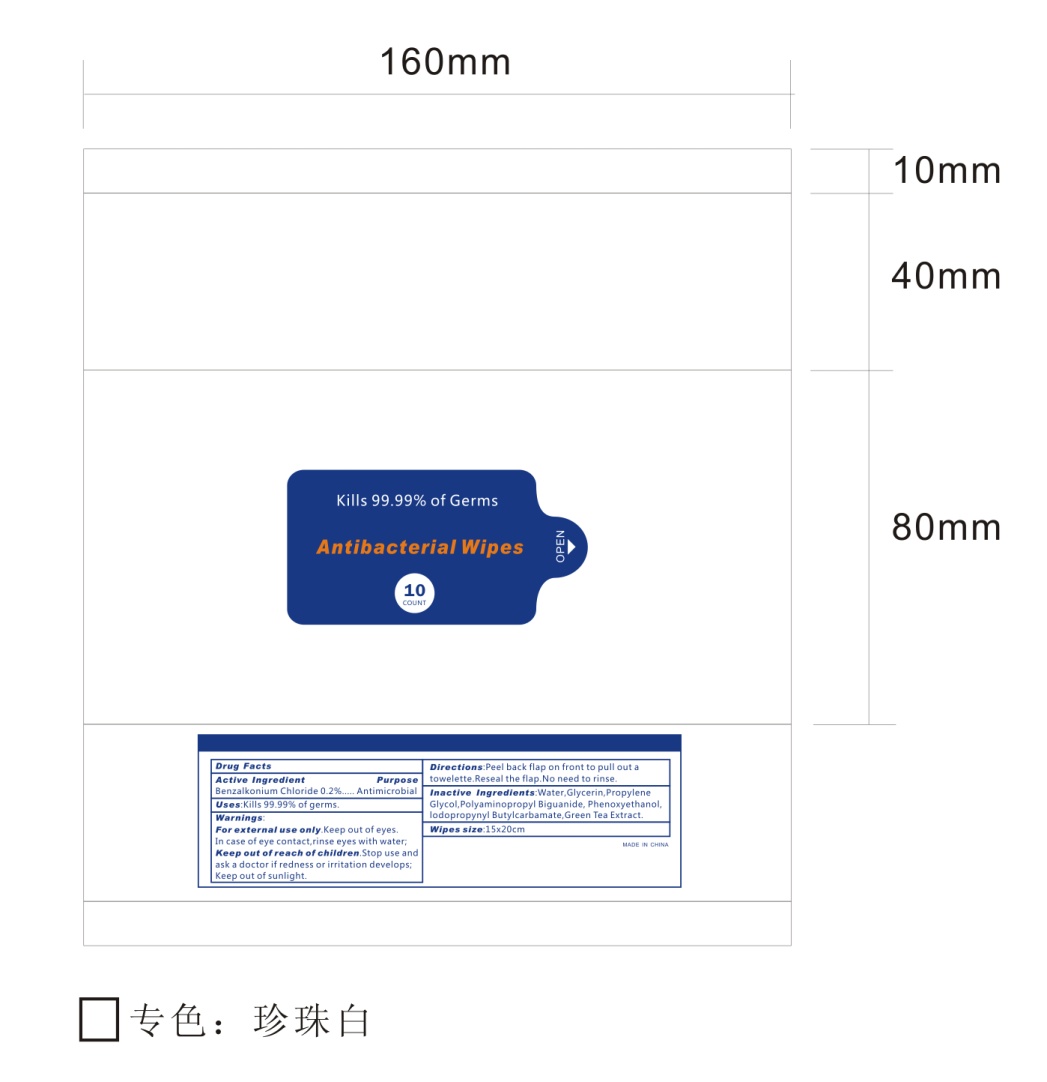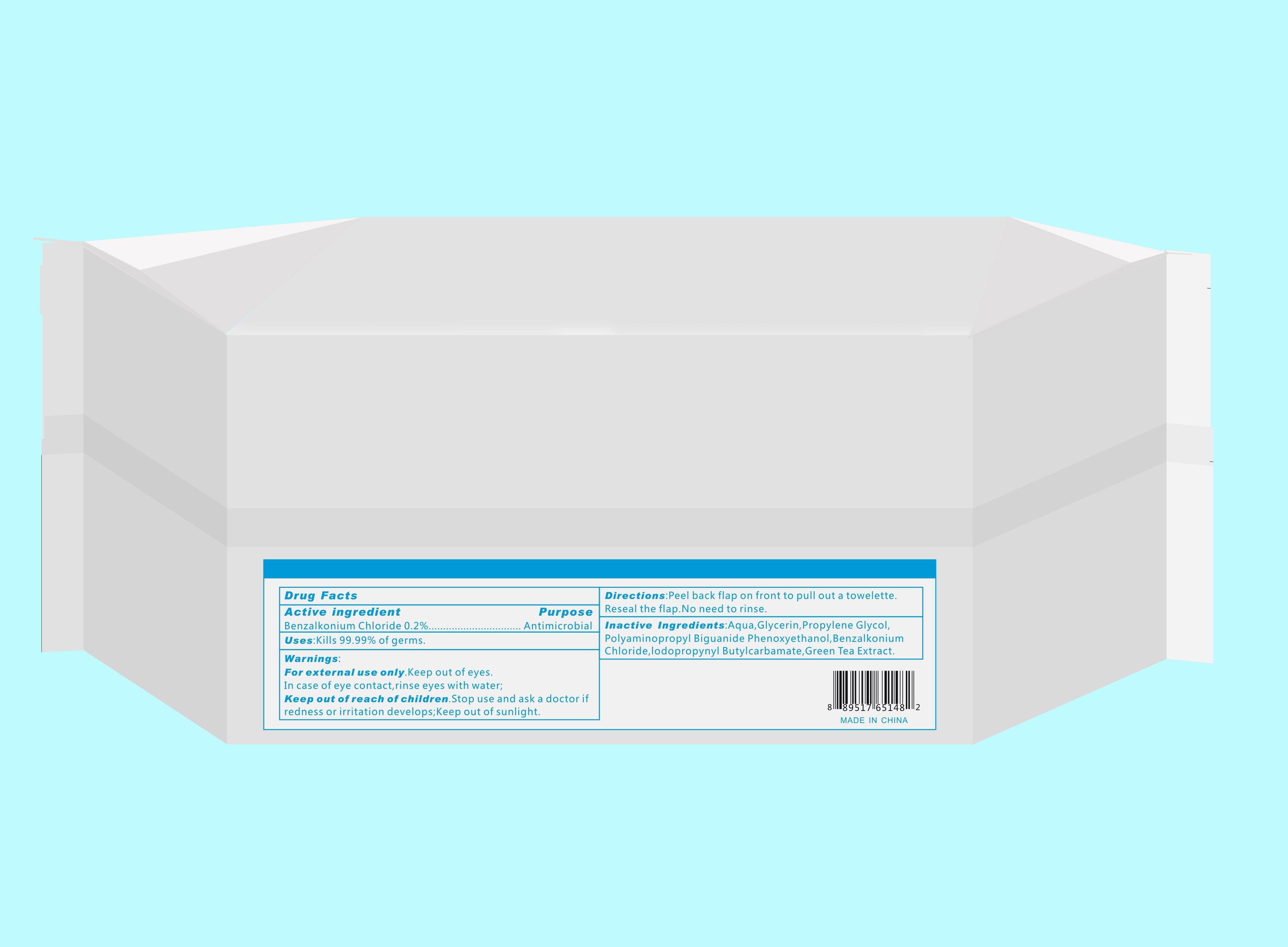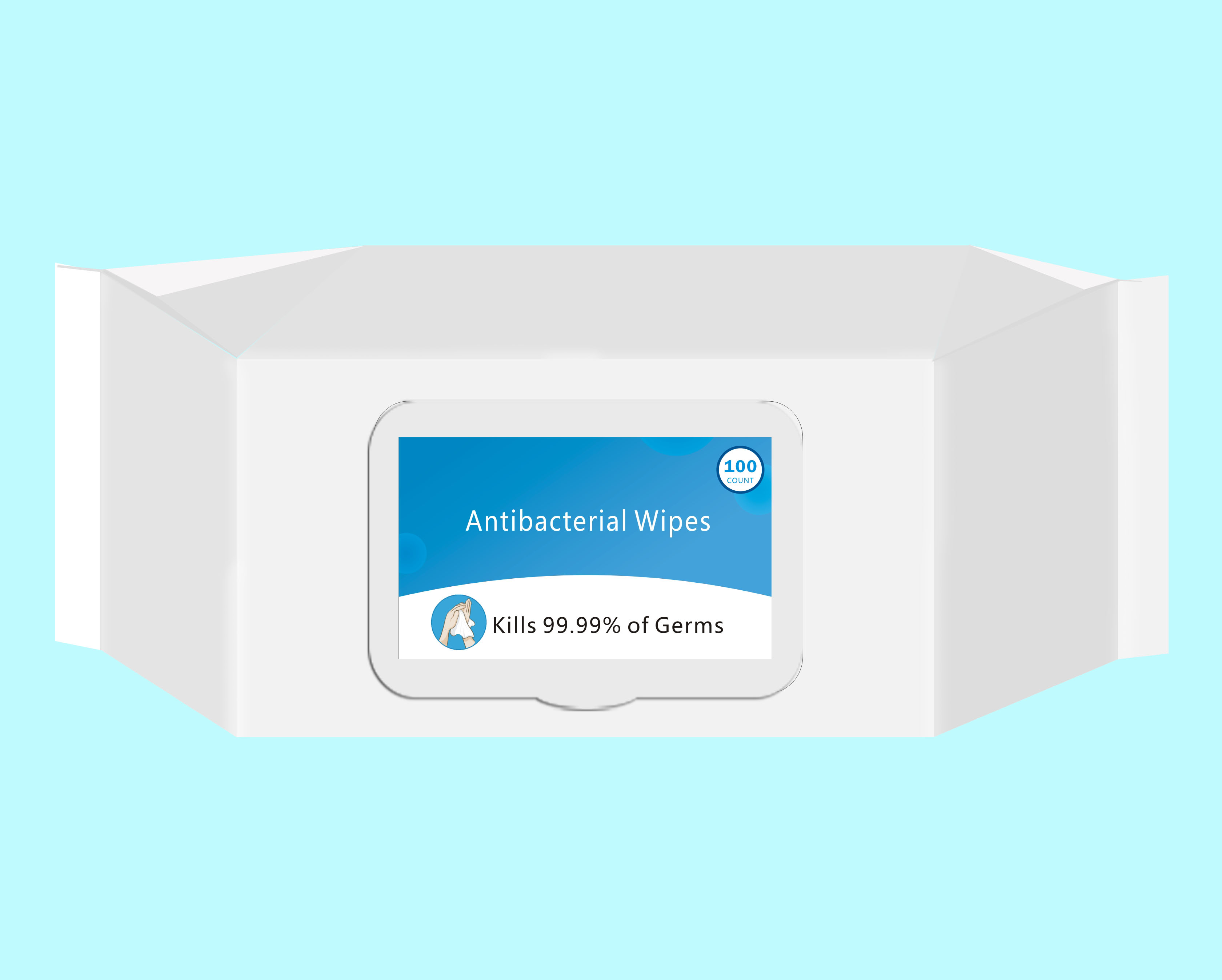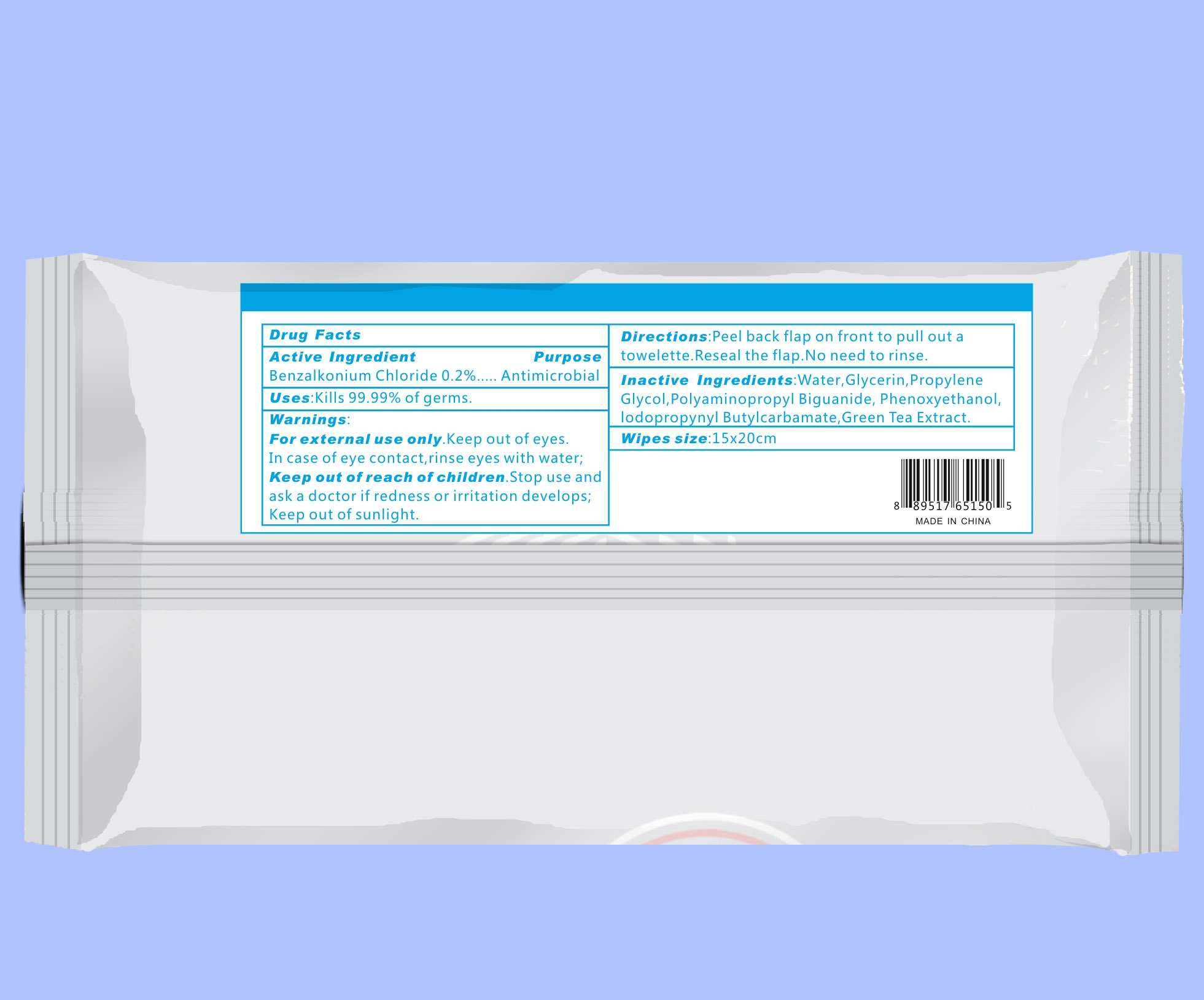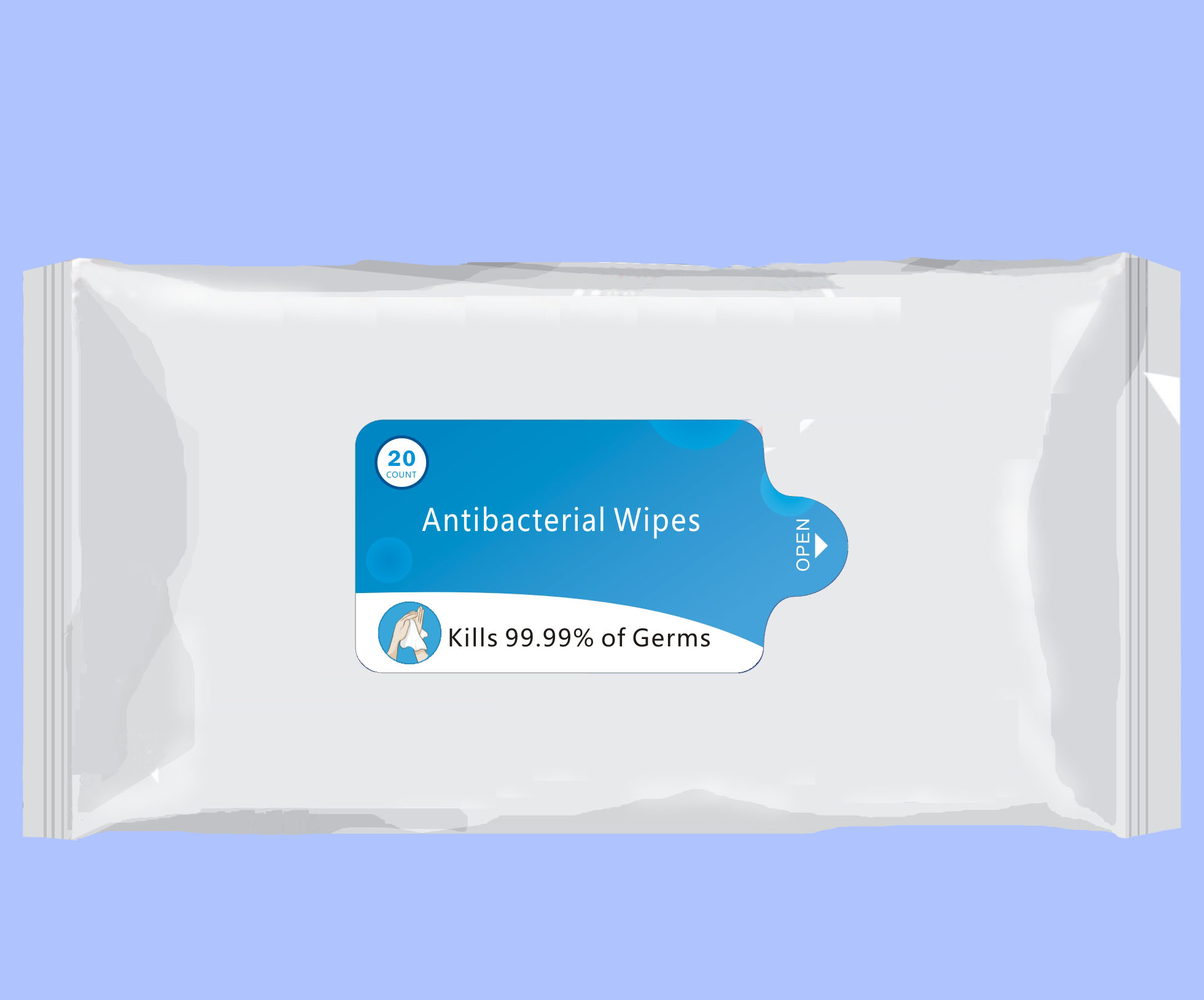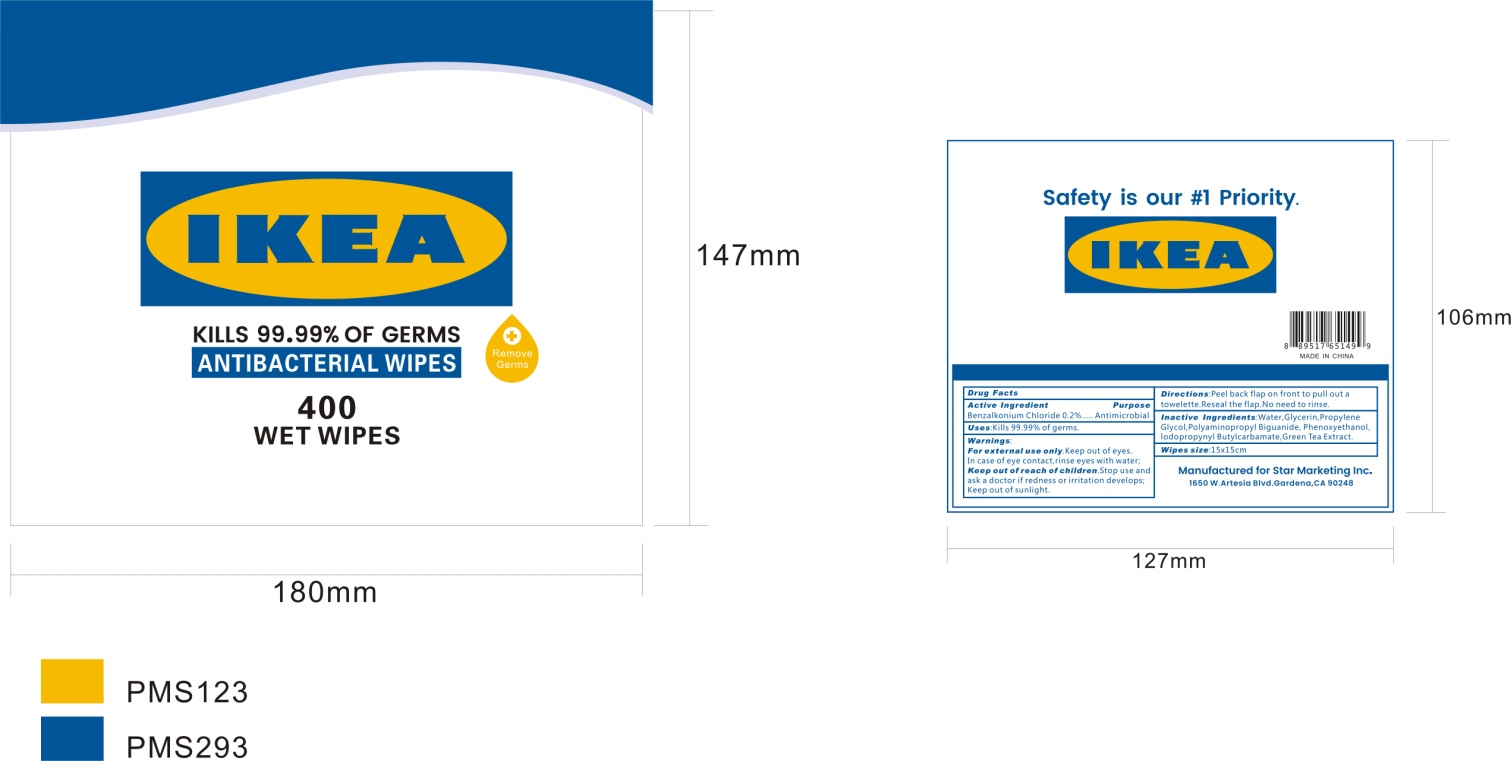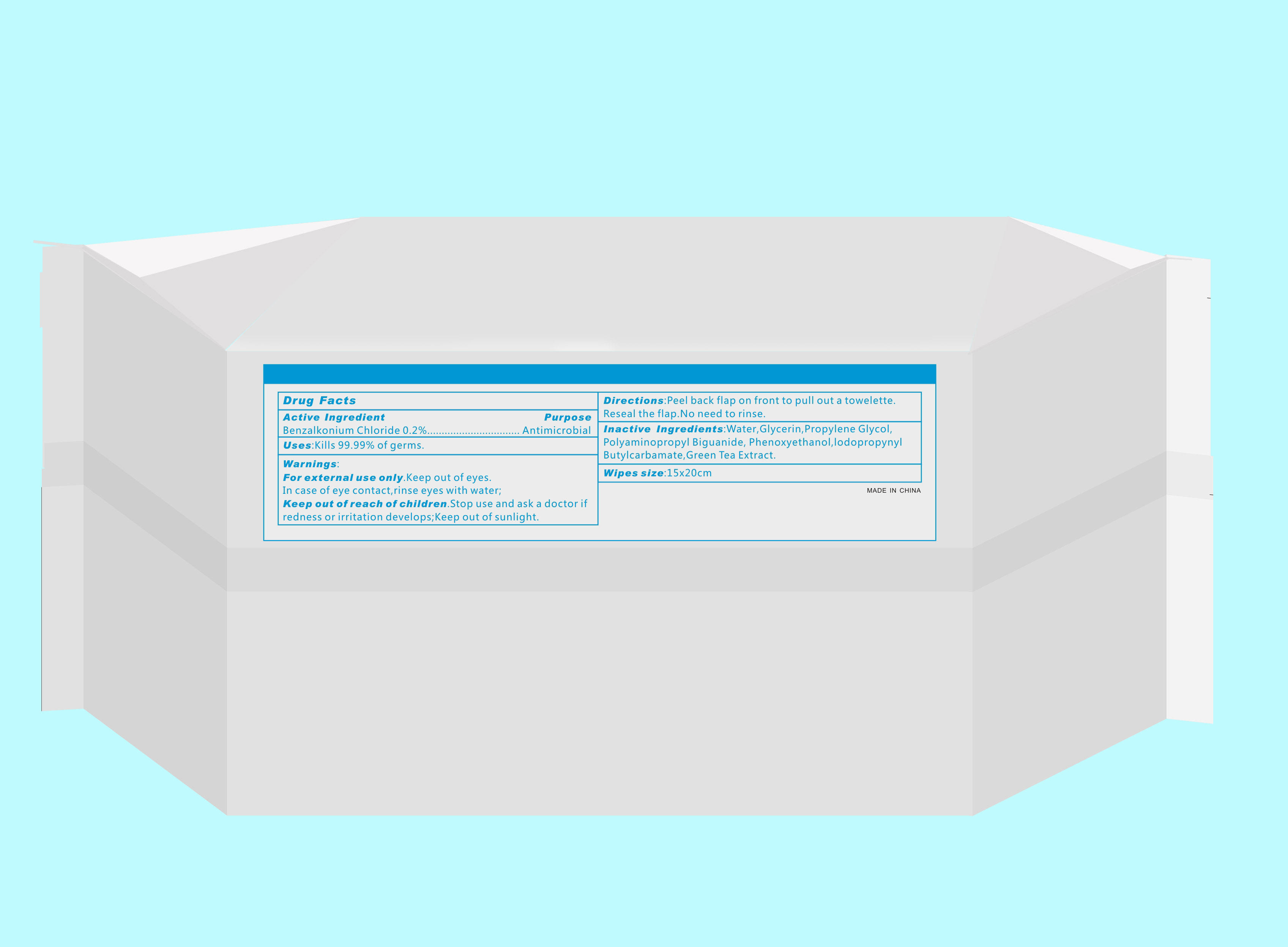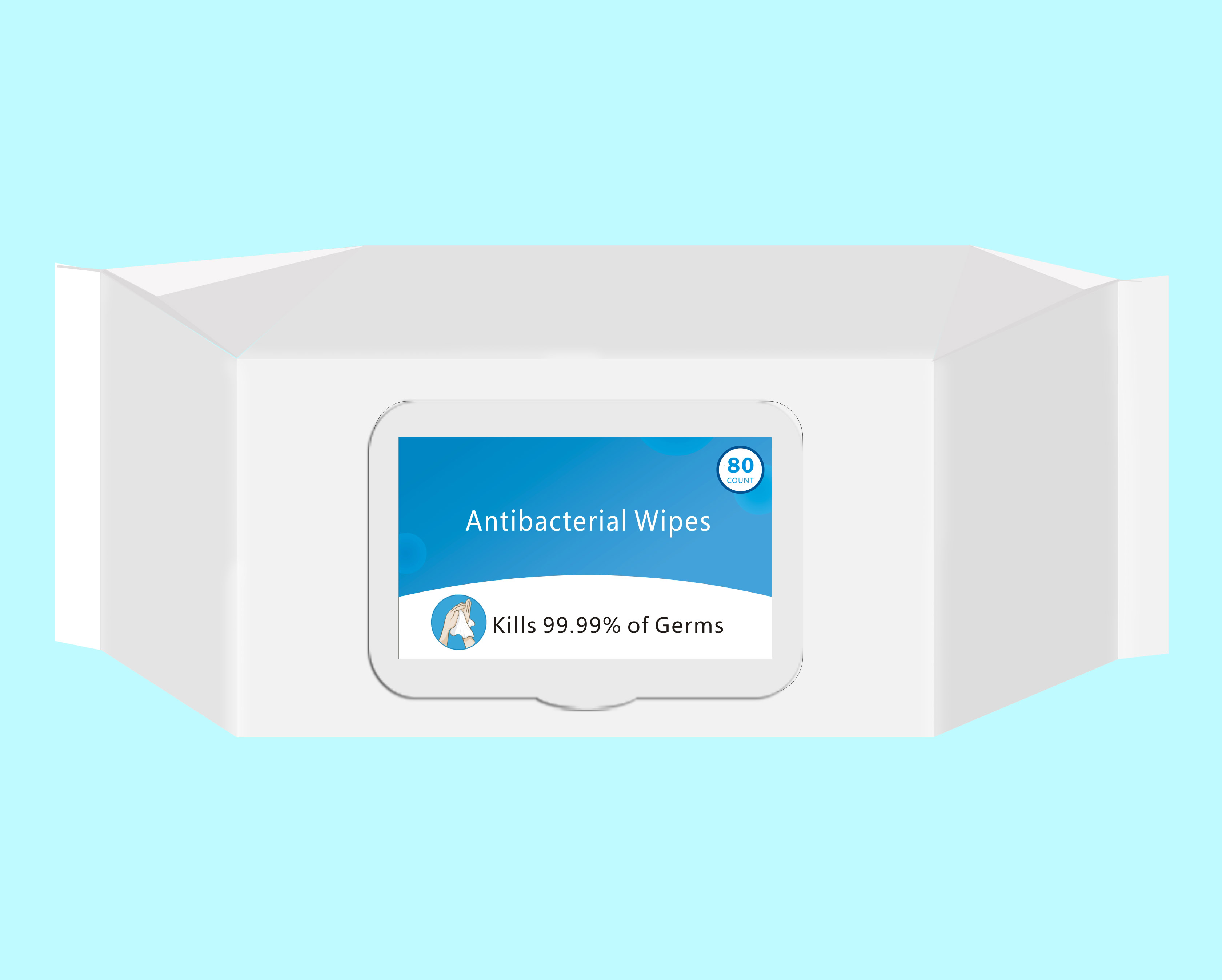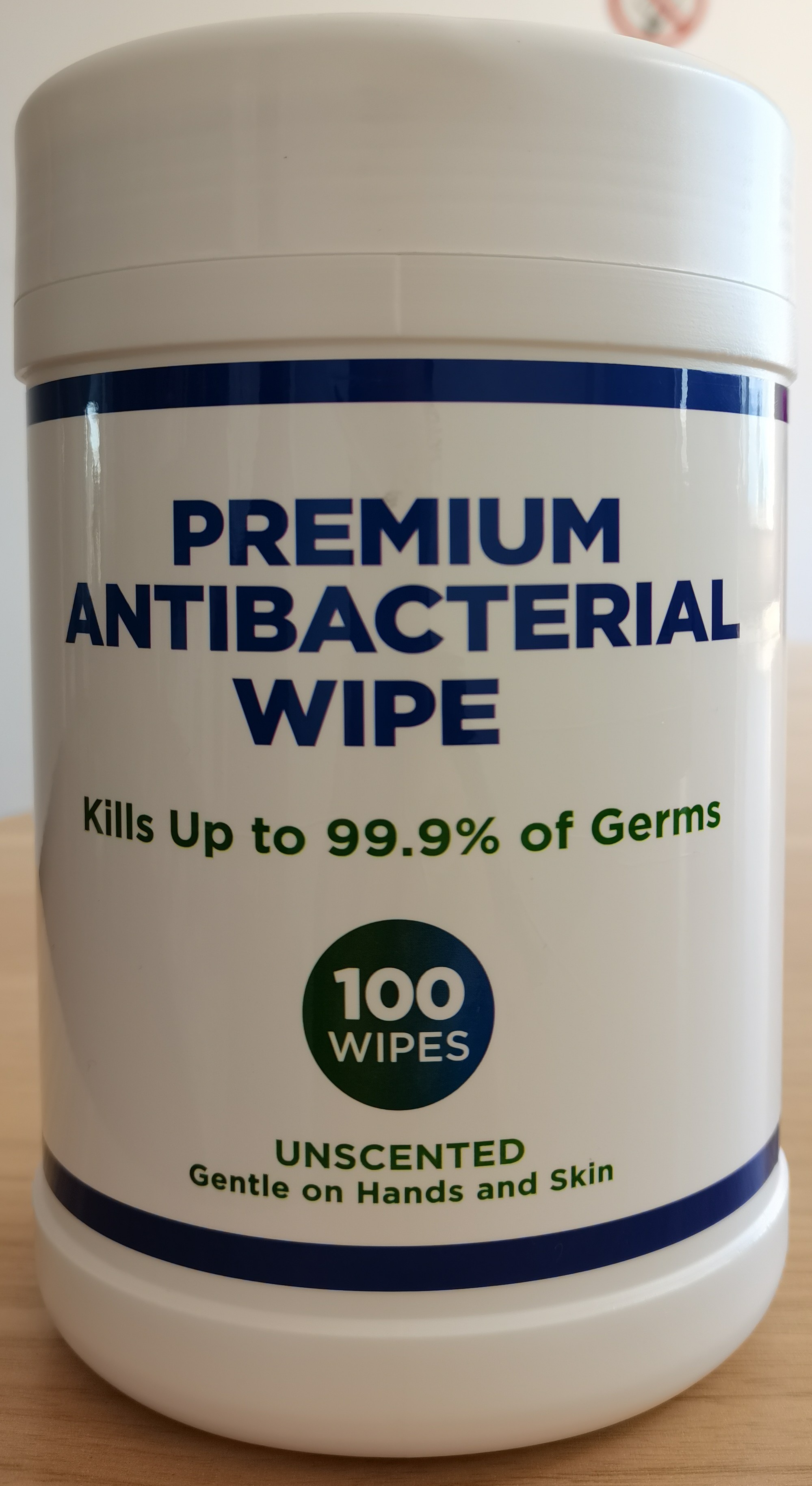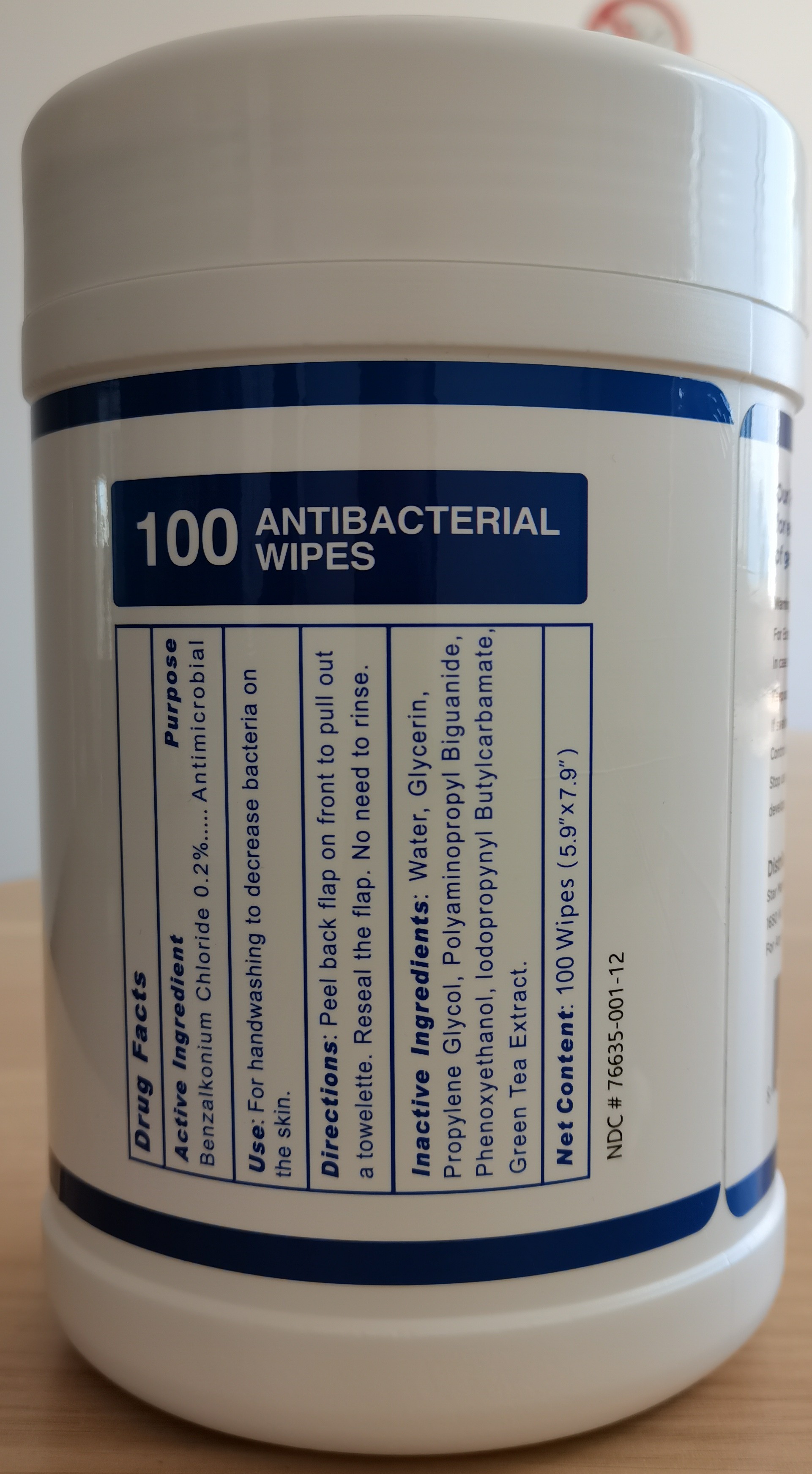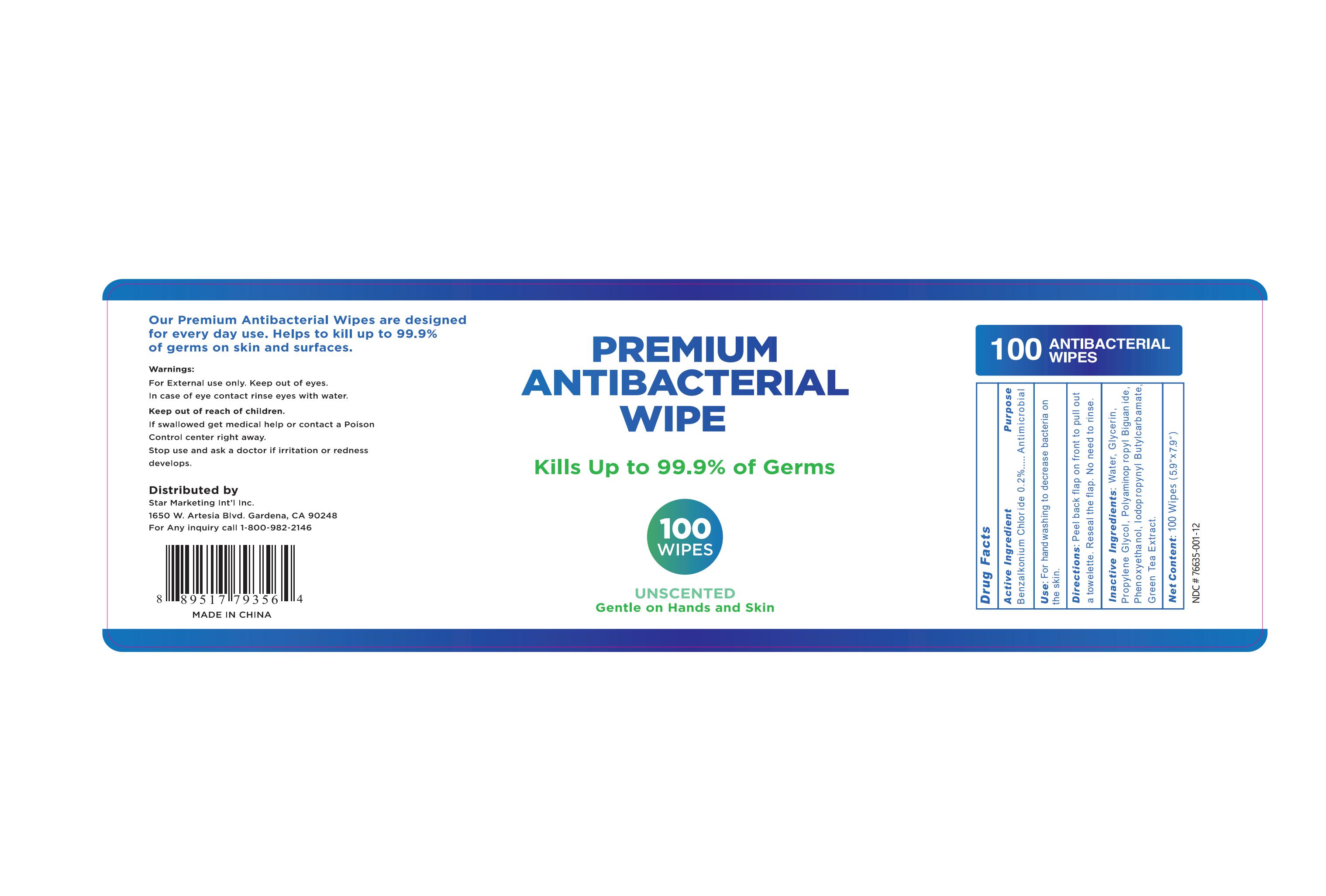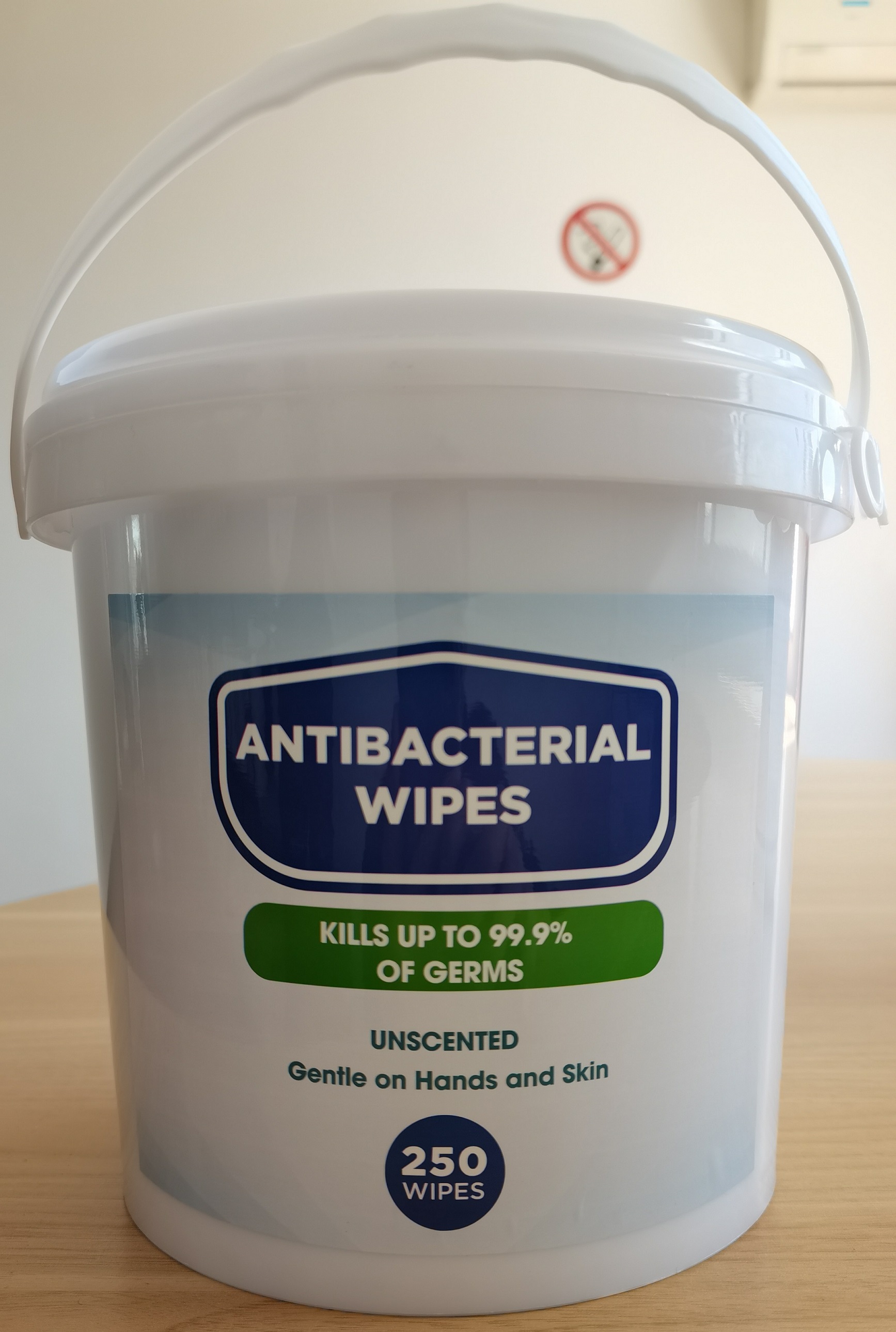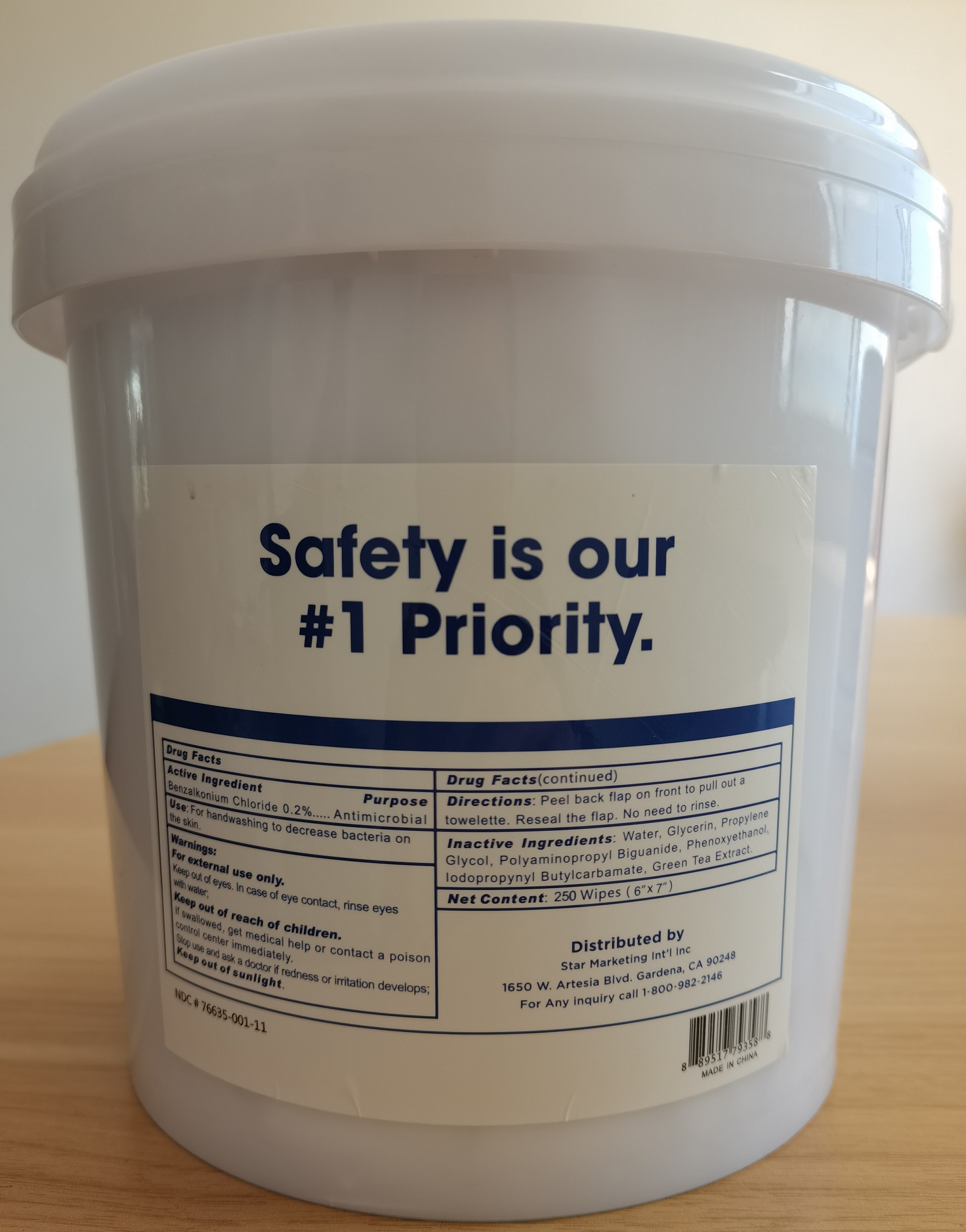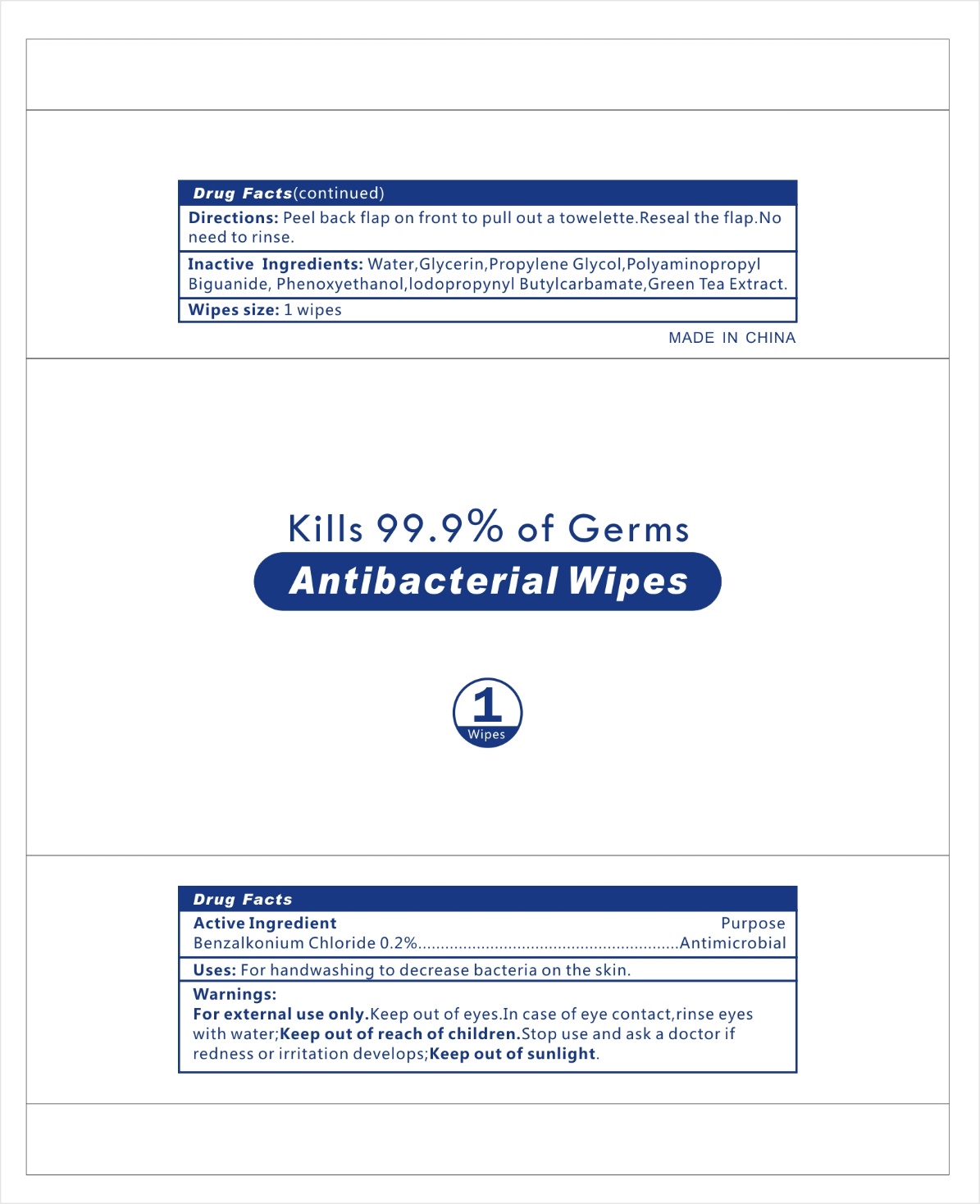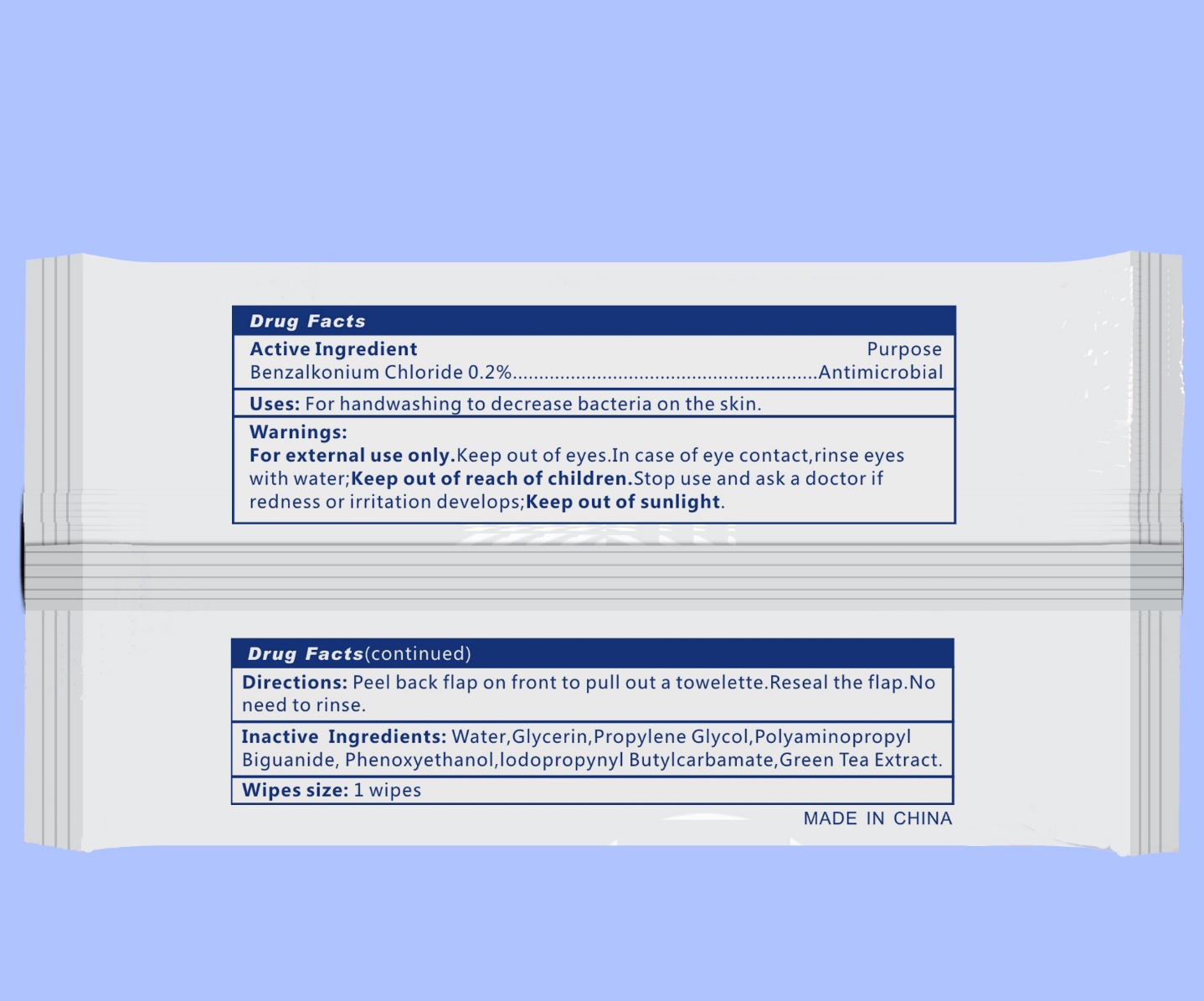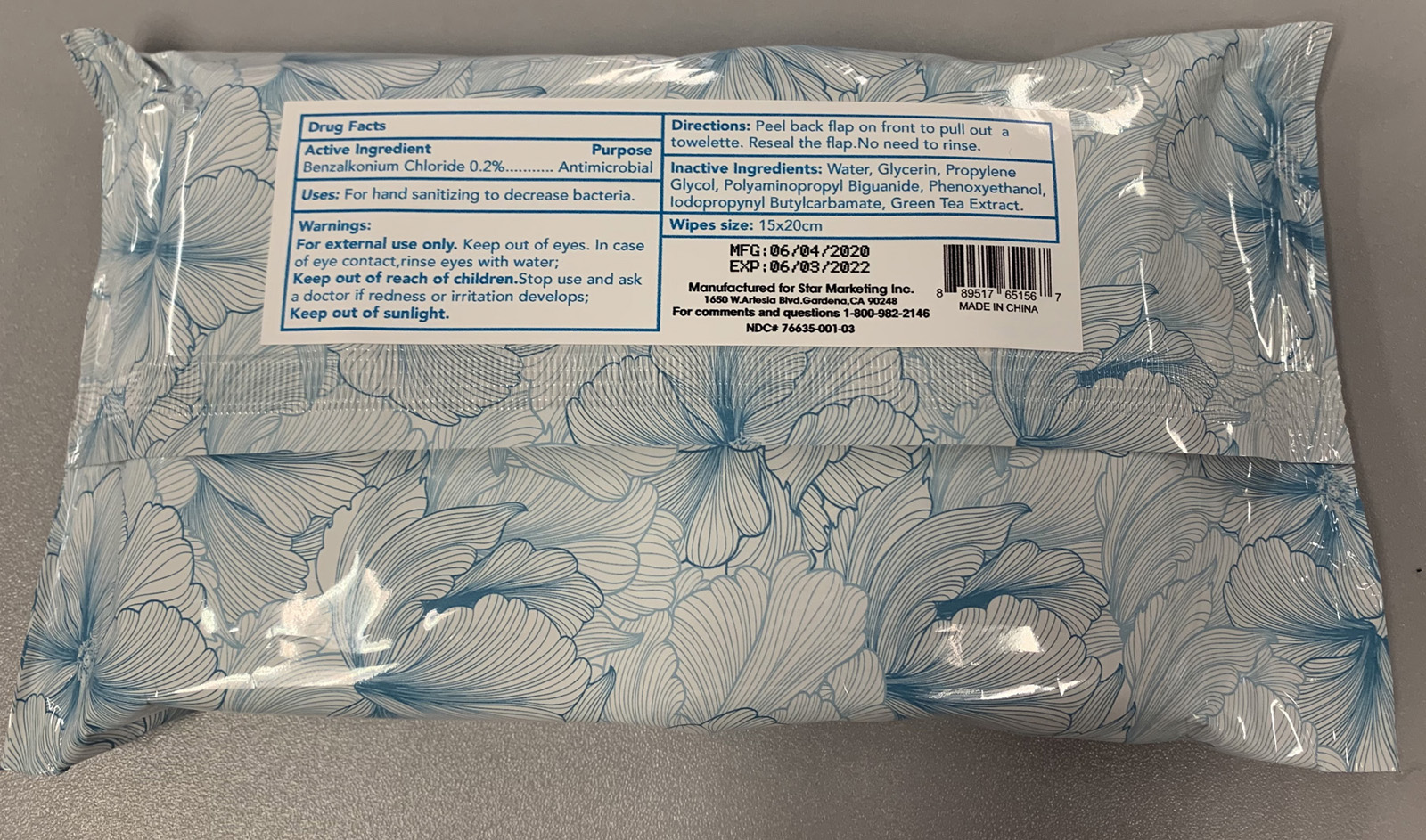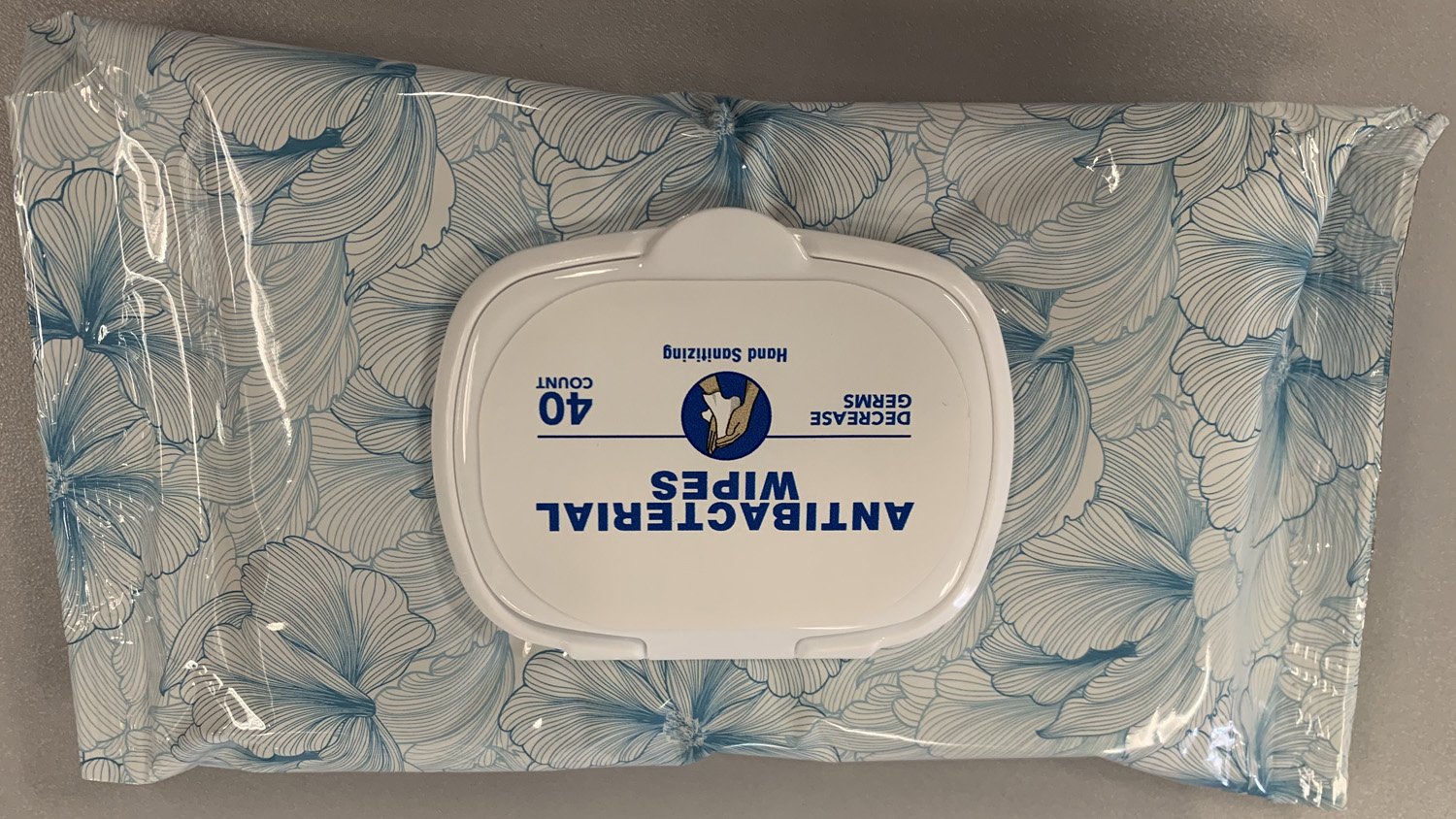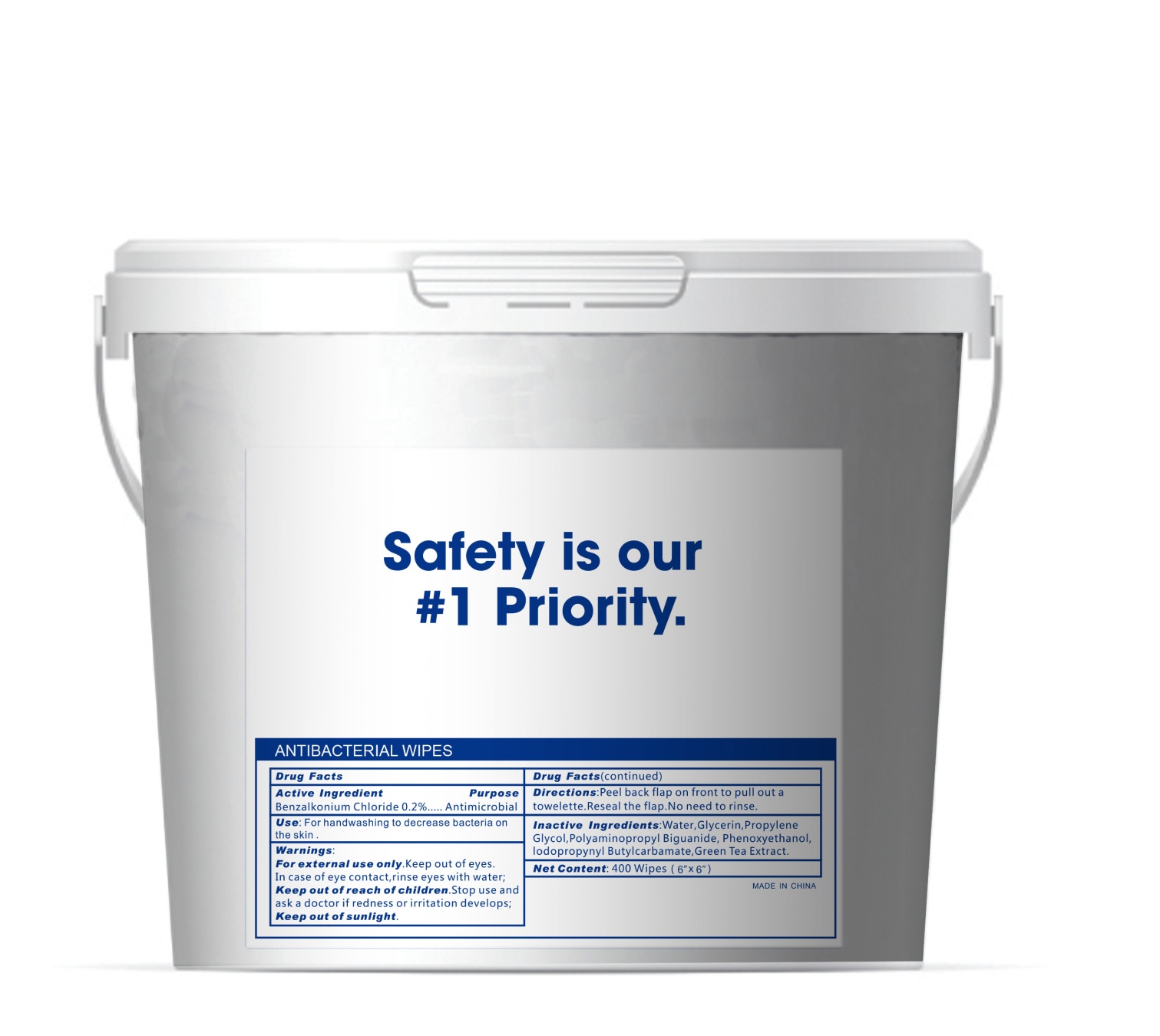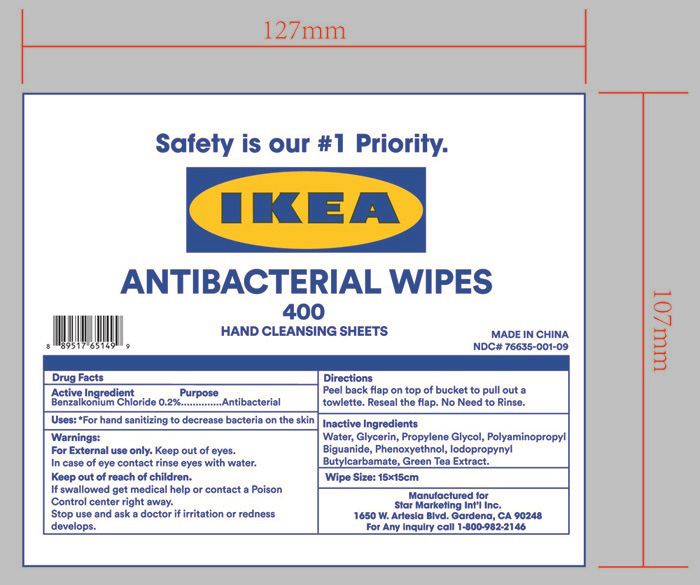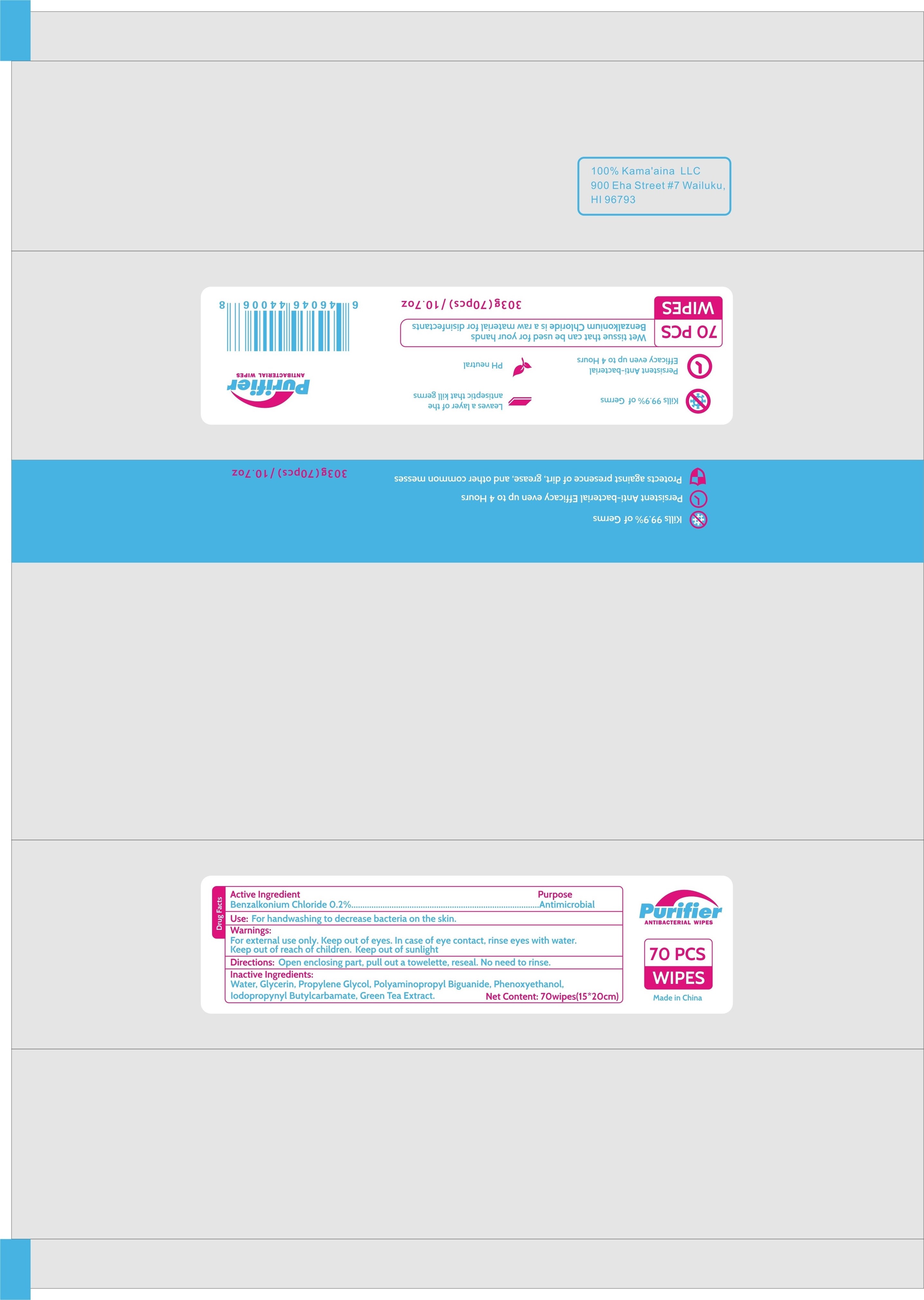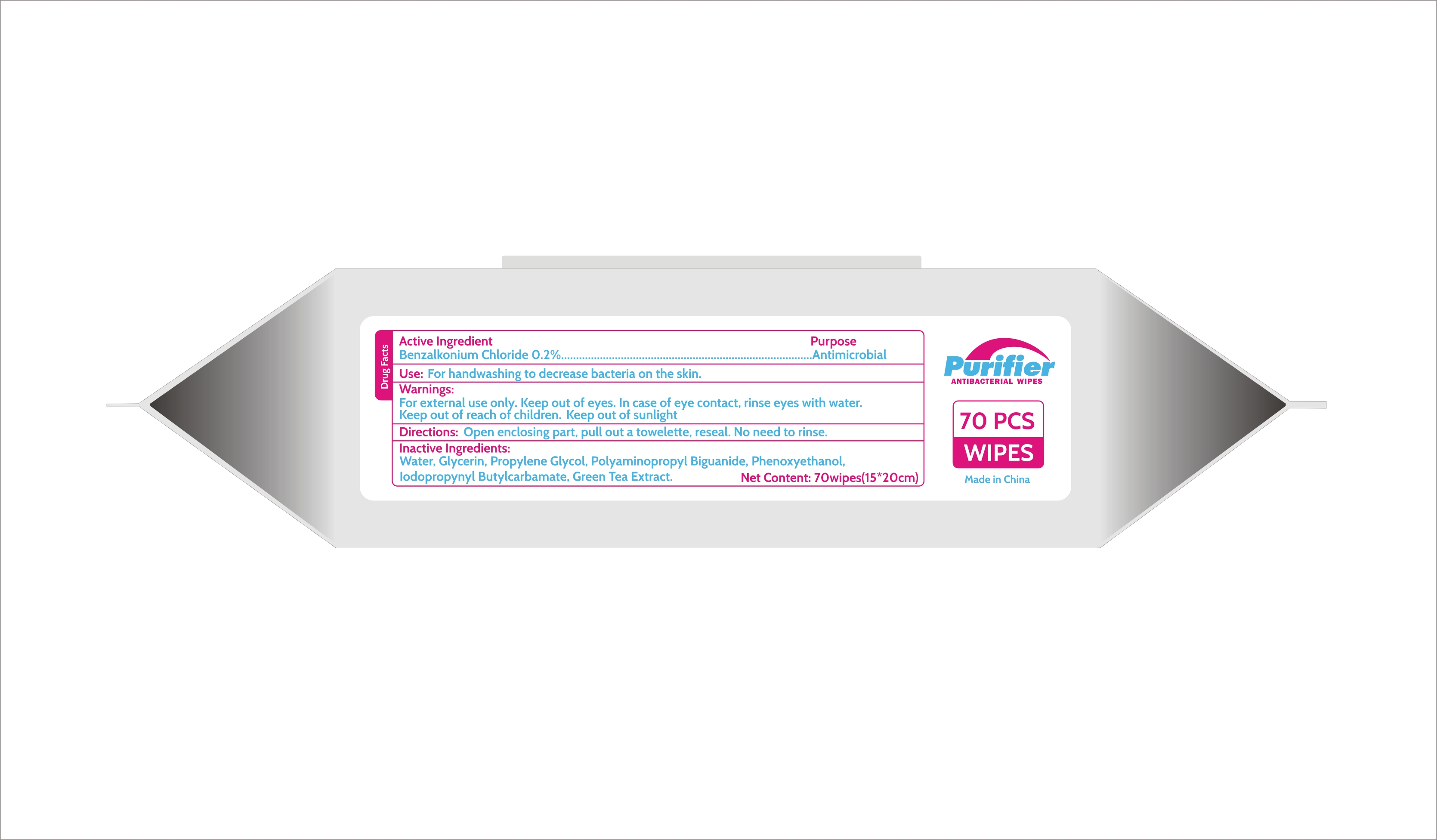 DRUG LABEL: Antibacterial Wipes
NDC: 76635-001 | Form: CLOTH
Manufacturer: Hangzhou Glamcos Biotech CO.,LTD
Category: otc | Type: HUMAN OTC DRUG LABEL
Date: 20231123

ACTIVE INGREDIENTS: BENZALKONIUM CHLORIDE 0.2 g/100 g
INACTIVE INGREDIENTS: POLYAMINOPROPYL BIGUANIDE; GLYCERIN; PROPYLENE GLYCOL; WATER; GREEN TEA LEAF; PHENOXYETHANOL; IODOPROPYNYL BUTYLCARBAMATE

Active Ingredient(s)

Benzalkonium Chloride 0.2%

Purpose

Antimicrobial

Use

Kills 99.99% of germs.

Warnings

For external use only. Keep out of eyes.
In case of eye contact, rinse eyes with water.

Stop use and ask a doctor if redness or irritation develops.
Keep out of sunlight.

Keep out of reach of children.

Directions

Peel back flap on front to pull out a towelette. Reseal the flap. No need ro rinse.

Inactive ingredients

Water，Glycerin，Propylene Glycol，Polyaminopropyl Biguanide，Phenoxyethanol ，Iodopropynyl Butylcarbamate，Green Tea Extract.

400 Pail Label - Principal Display Panel

NDC:76635-001-06

NDC:76635-001-07

NDC:76635-001-09

250 Pail Package Label - Principal Display Panel

NDC:76635-001-11

100 Pail Package Label - Principal Display Panel

NDC:76635-001-12